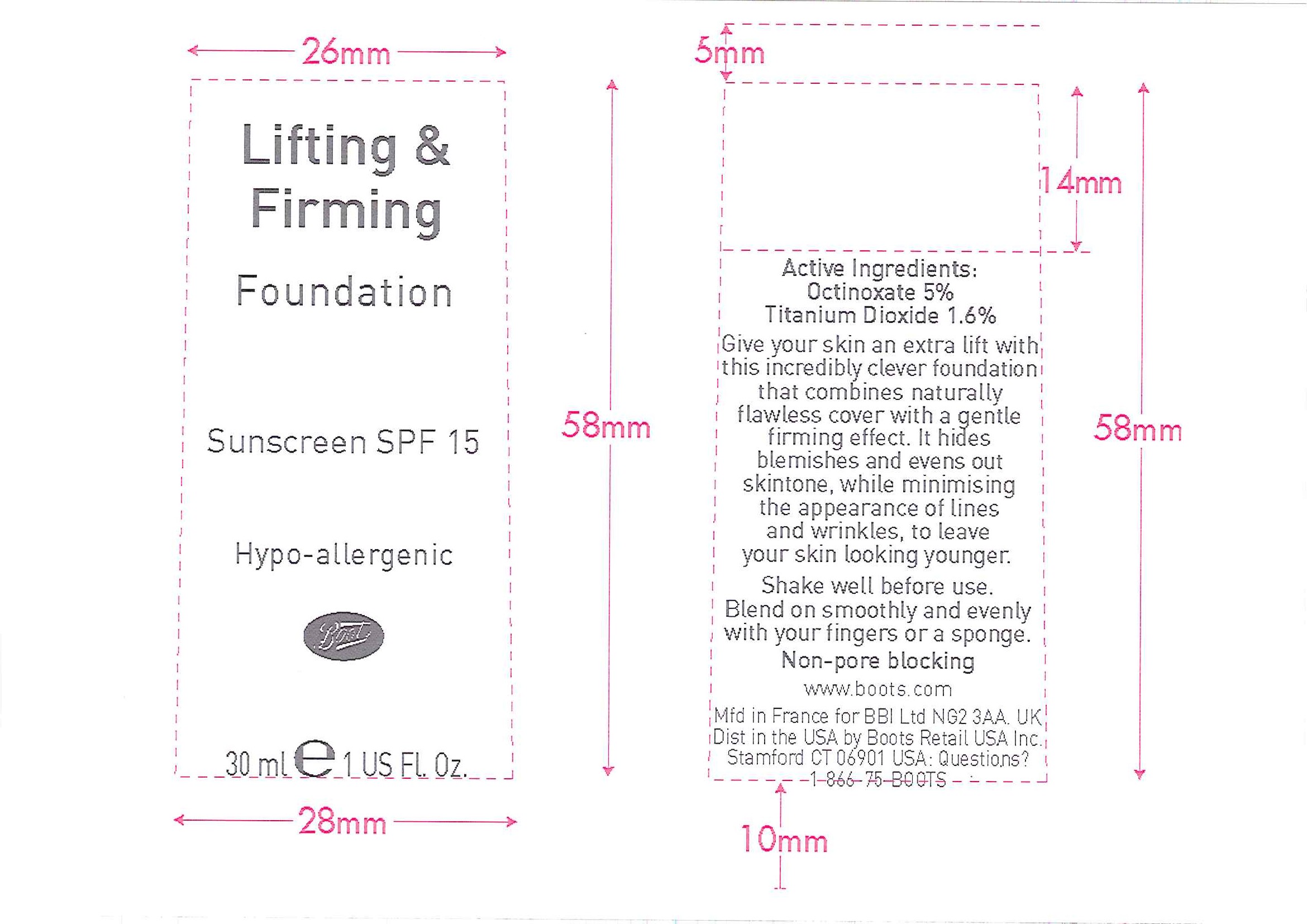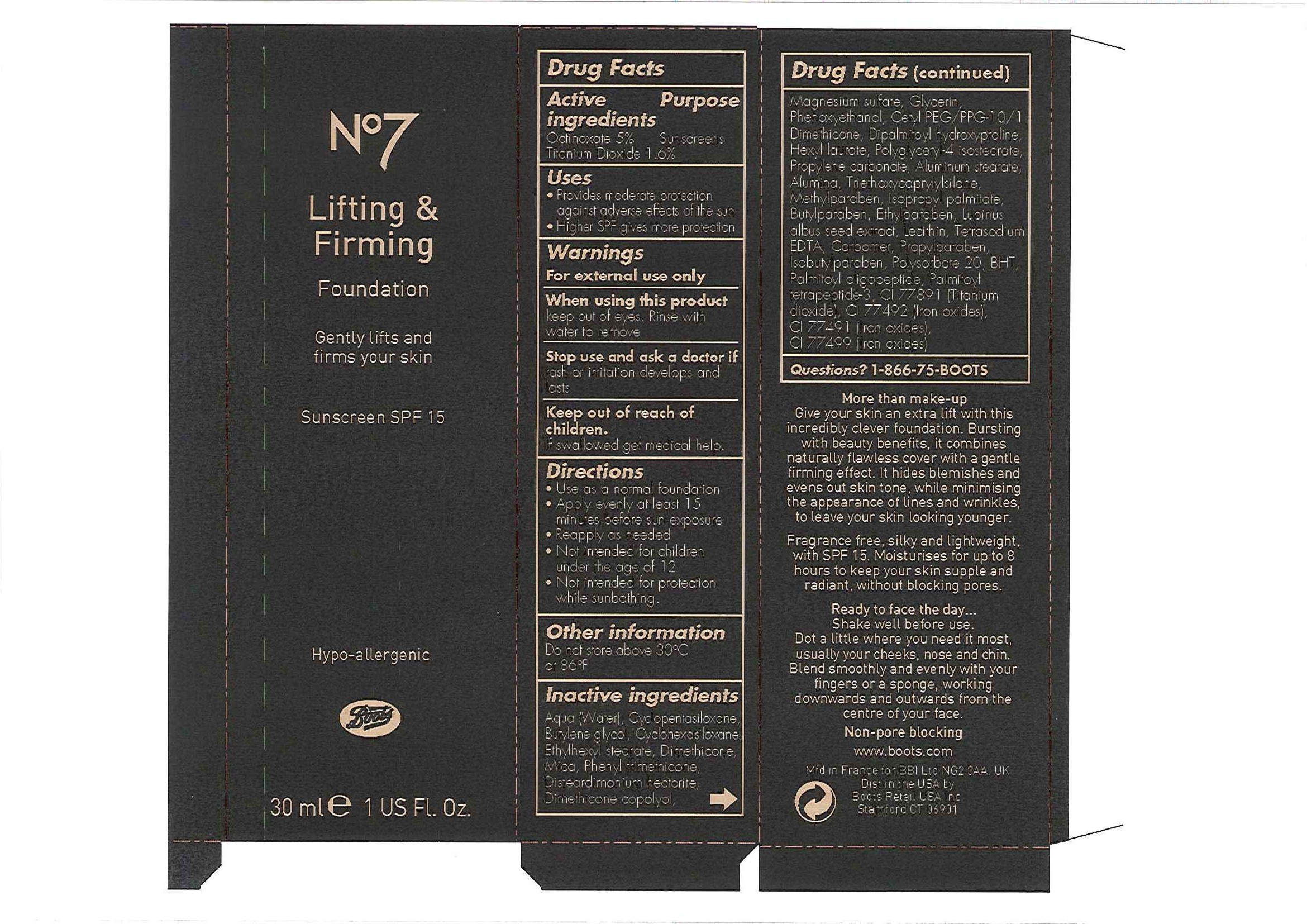 DRUG LABEL: No7 Lifting and Firming Foundation Sunscreen SPF 15 Porcelain
NDC: 61589-3809 | Form: EMULSION
Manufacturer: BCM Cosmetique SAS
Category: otc | Type: HUMAN OTC DRUG LABEL
Date: 20101207

ACTIVE INGREDIENTS: OCTINOXATE 1.5 mL/30 mL; TITANIUM DIOXIDE 0.48 mL/30 mL
INACTIVE INGREDIENTS: WATER; CYCLOMETHICONE 5; BUTYLENE GLYCOL; CYCLOMETHICONE 6; DIMETHICONE; PHENYL TRIMETHICONE; MAGNESIUM SULFATE, UNSPECIFIED; GLYCERIN; PHENOXYETHANOL; HEXYL LAURATE; PROPYLENE CARBONATE; ALUMINUM STEARATE; ALUMINUM OXIDE; OCTYLTRIETHOXYSILANE; METHYLPARABEN; ISOPROPYL PALMITATE; BUTYLPARABEN; ETHYLPARABEN; LECITHIN, SOYBEAN; CARBOMER HOMOPOLYMER TYPE C; PROPYLPARABEN; POLYSORBATE 20; BUTYLATED HYDROXYTOLUENE; FERRIC OXIDE YELLOW; FERRIC OXIDE RED; FERROSOFERRIC OXIDE

Carton and bottle labelling

Active Ingredients Purpose

Octinoxate 5% Sunscreens

Titanium Dioxide 1.6%

Uses

- Provides moderate protection against adverse effects of the sun
- Higher SPF gives more protection

Warnings

For external use only

When using this product

Keep out of eyes. Rinse with water to remove.

Stop use and ask a doctor if rash or irritation develops and lasts

Keep out of reach of children.

If swallowed get medical help.

Directions

- Use as a normal foundation
- Apply evenly at least 15 minutes before sun exposure
- Reapply as needed
- Not intended for children under the age of 12
- Not intended for protection while sunbathing

Other information

Do not store above 30oC or 86oF

Inactive ingredients

Aqua (Water), Cyclopentasiloxane, Butylene glycol, Cyclohexasiloxane, Ethylhexyl stearate, Dimethicone, Mica, Phenyl trimethicone, Disteardimonium hectorite, Dimethicone copolyol, Magnesium sulfate, Glycerin, Phenoxyethanol, Cetyl PEG/PPG-10/1 Dimethicone, Dipalmitoyl hydroxyproline, Hexyl laurate, Polyglyceryl-4 isostearate, Propylene carbonate, Aluminum stearate, Alumina, Triethoxycaprylylsilane, Methylparaben, Isopropyl palmitate, Butylparaben, Ethylparaben, Lupinus albus seed extract, Lecithin, Tetrasodium EDTA, Carbomer, Propylparaben, Isobutylparaben, Polysorbate 20, BHT, Palmitoyl oligopeptide, Palmitoyl tetrapeptide-3, CI 77891 (Titanium dioxide), CI 77492 (Iron oxides), CI 77491 (Iron oxides), CI 77499 (Iron oxides)

Questions? 1-866-75-BOOTS

DESCRIPTION

More than make-up

Give your skin an extra lift with this incredibly clever foundation. Bursting with beauty benefits, it combines naturally flawless cover with a gentle firming effect. It hides blemishes and evens out skin tone, while minimising the appearance of lines and wrinkles, to leave your skin looking younger.

Fragrance free, silky and lightweight, with SPF 15. Moisturises for up to 8 hours to keep your skin supple and radiant, without blocking pores.

Ready to face the day ...

Shake well before use.
Dot a little where you need it most, usually your cheeks, nose and chin. Blend smoothly and evenly with your fingers or a sponge, working downwards and outwards from the centre of your face.

Non-pore blocking

PATIENT COUNSELING INFORMATION

www.boots.com

Mfd in France for BBI Ltd NG2 3AA. UK

Dist in the USA by Boots Retail USA Inc Stamford CT 06901

ACTIVE INGREDIENT

Bottle label
Active Ingredients:
Octinoxate 5%
Titanium Dioxide 1.6%

DESCRIPTION

Give your skin an extra lift with this incredibly clever foundation that combines naturally flawless cover with a gentle firming effect. It hides blemishes and evens out skintone, while minimising the appearance of lines and wrinkles, to leave your skin looking younger.

Shake well before use. Blend on smoothly and evenly with your fingers or a sponge.

Non-pore blocking.

PATIENT COUNSELING INFORMATION

www.boots.com

Mfd in France for BBI Ltd NG2 3AA. UK

Dist in the USA by Boots Retail USA Inc. Stamford CT 06901

USA: Questions? 1-866-75-BOOTS

Carton label

No7

Lifting and Firming

Foundation

Gently lifts and firms your skin

Sunscreen SPF 15

Hypo-allergenic

Boots

30ml e 1 US Fl. Oz

Lifting and Firming Fnd Porcelain carton.jpg

Bottle label

Lifting and Firming

Foundation

Sunscreen SPF 15

Hypo-allergenic

Boots

30ml e 1 US Fl. Oz

Lifting and Firming Fdn Porcelain bottle labels.jpg